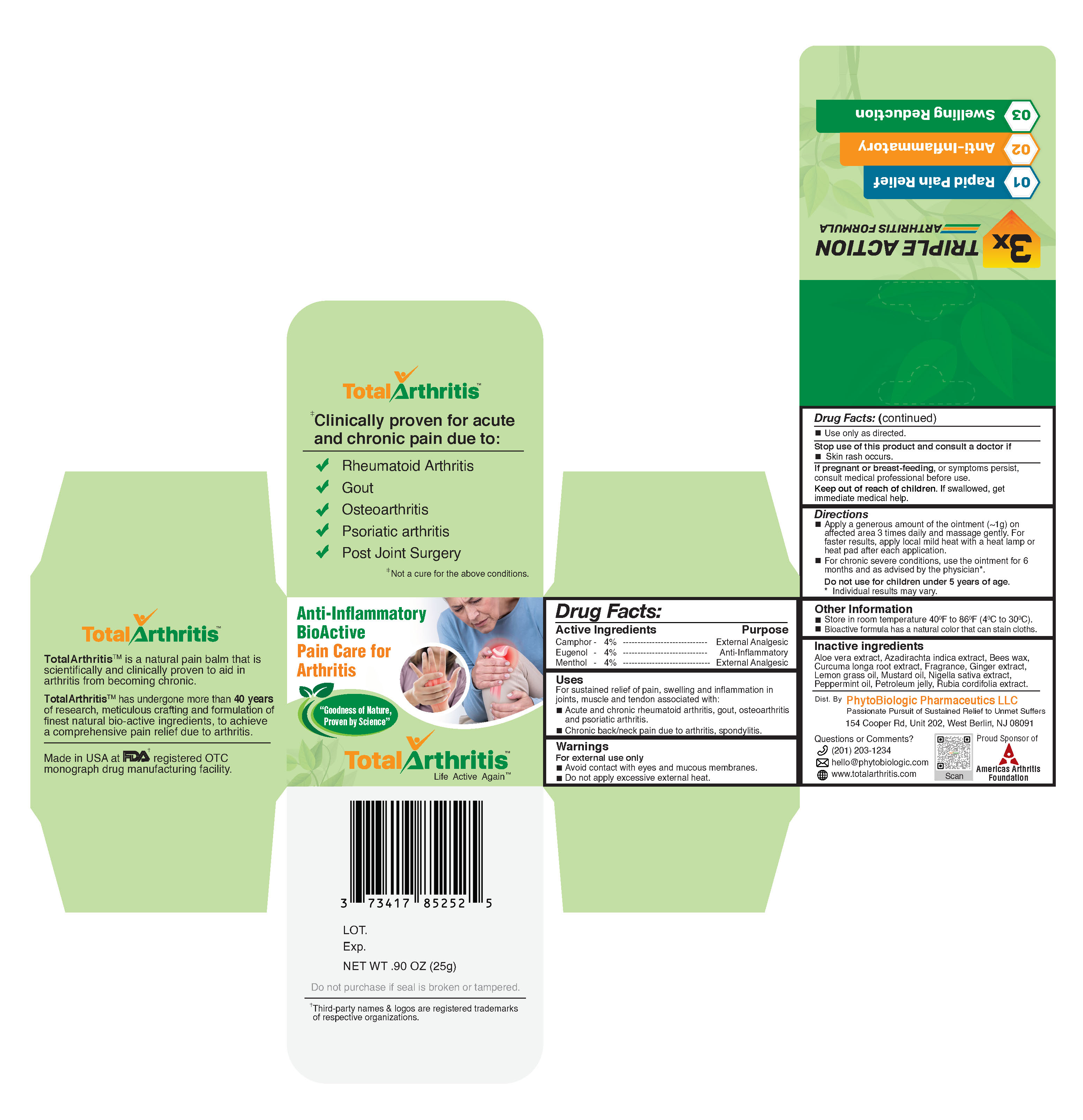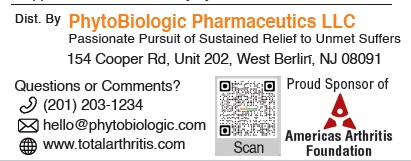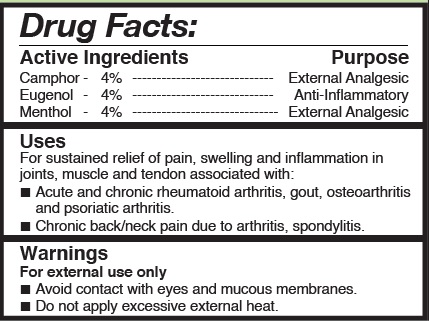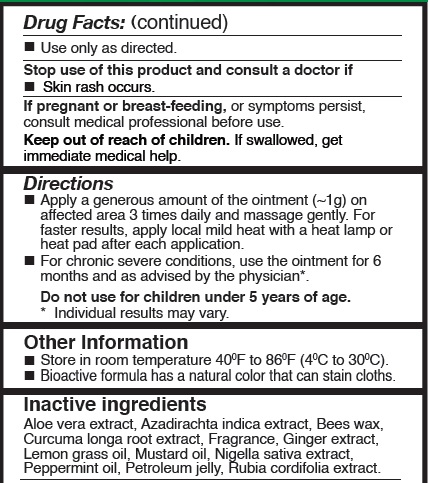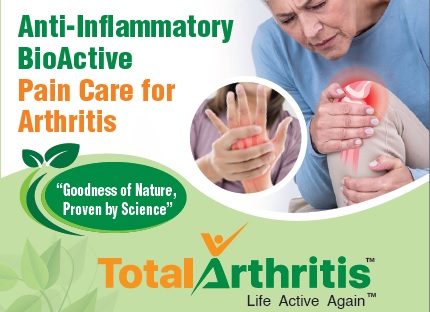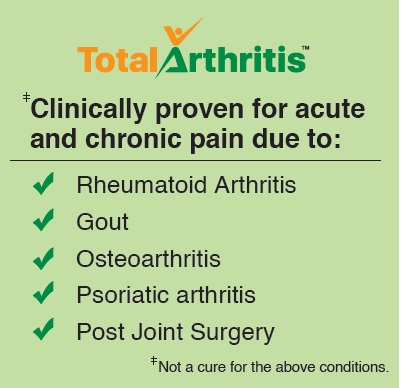 DRUG LABEL: TotalArthritis
NDC: 73417-852 | Form: OINTMENT
Manufacturer: PhytoBiologic Pharmaceutics LLC
Category: otc | Type: HUMAN OTC DRUG LABEL
Date: 20210724

ACTIVE INGREDIENTS: CAMPHOR (NATURAL) 40 mg/1 g; EUGENOL 40 mg/1 g; MENTHOL 40 mg/1 g
INACTIVE INGREDIENTS: NIGELLA SATIVA SEED; EAST INDIAN LEMONGRASS OIL; MUSTARD OIL; PETROLATUM; PEPPERMINT OIL; AZADIRACHTA INDICA LEAF; YELLOW WAX; RUBIA CORDIFOLIA ROOT; ALOE VERA LEAF; TURMERIC; GINGER

TotalArthritis - Pain Care for Acute and Chronic Arthritis

TotalArthritis Active Ingredients

Camphor | 4% | External Analgesic
Eugenol | 4% | Anti-Inflammatory
Menthol | 4% | External Analgesic

Purpose

Camphor | External Analgesic
Eugenol | Anti-inflammatory
Menthol | External Analgesic

Uses

For sustained relief of pain, swelling and Inflammation in joints, muscle and tendon associated with:
• Acute and chronic rheumatoid arthritis, gout, osteoarthritis and psoriatic arthritis.
• Chronic back/neck pain due to arthritis, spondylitis.

Warnings for external use only

- Avoid contact with eyes and mucous membranes.
- Do not apply excessive external heat.
- Use only as directed.

When using this product

- Do not apply excessive external heat
- Avoid contact with eyes and mucous membranes.

Stop use of this product and consult a doctor If

- Skin rash occurs

Directions

- Apply a generous amount of the ointment (~1g) on affected area 3 times daily and massage gently. For faster results, apply

local heat with a heat lamp or heat pad after each application.

- For chronic severe conditions, use the ointment for 6 to 9 months and as advised by the physician*.

* Individual results vary depending on the chronic conditions, age and time length of suffering.

Other information

- Store in room temperature 40^0F to 86^0F (4^0C to 30^0C)
- Bioactive formula has a natural color that can stain cloths

Inactive Ingredients

Aloe vera extract, Azadirachta indica extract, Bees wax,Curcuma longa root extract, Fragrance, Ginger extract, Lemon grass oil, Mustard oil, Nigella sativa extract, Peppermint oil, Petroleum jelly, Rubia cordifolia extract.

RECENT MAJOR CHANGES

- Active Ingredients (Camphor - 4%, Eugenol - 4%, Menthol - 4%)
- Do not apply excessive external heat.
- Do not use for children under 5 years of age.
- Inactive ingredients (Aloe vera extract, Azadirachta indica extract, Bees wax, Curcuma longa root extract, Fragrance, Ginger extract, Lemongrass oil, Mustard oil, Nigella sativa extract, Peppermint oil, Petroleum jelly, Rubia cordifolia extract.)